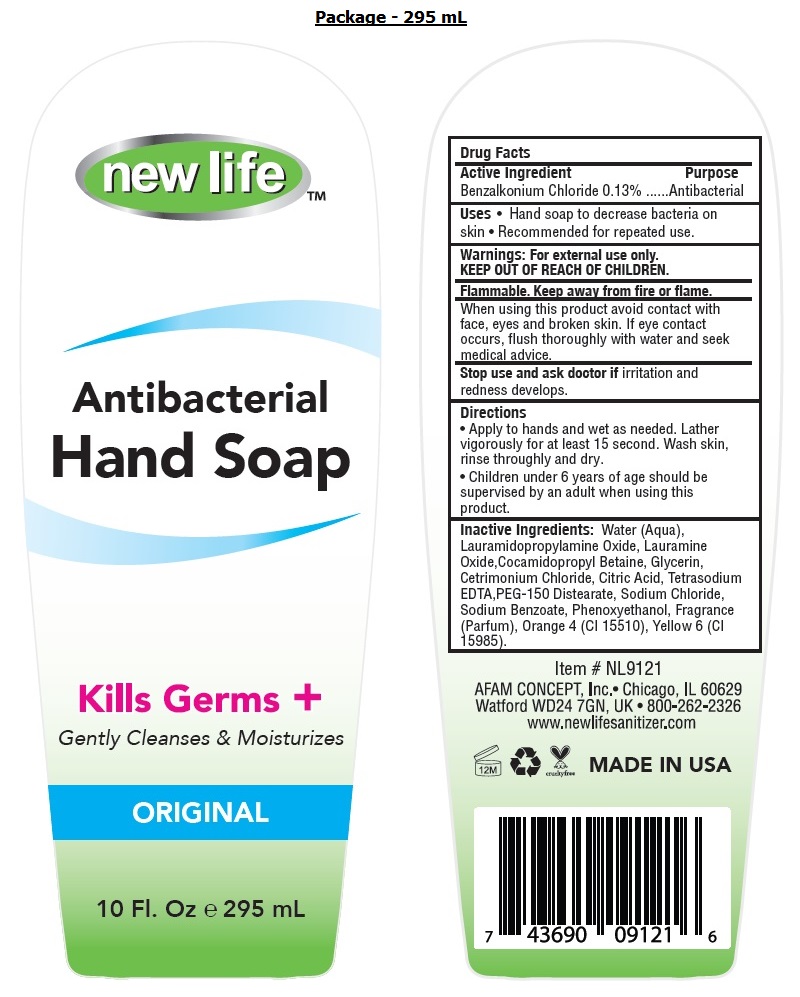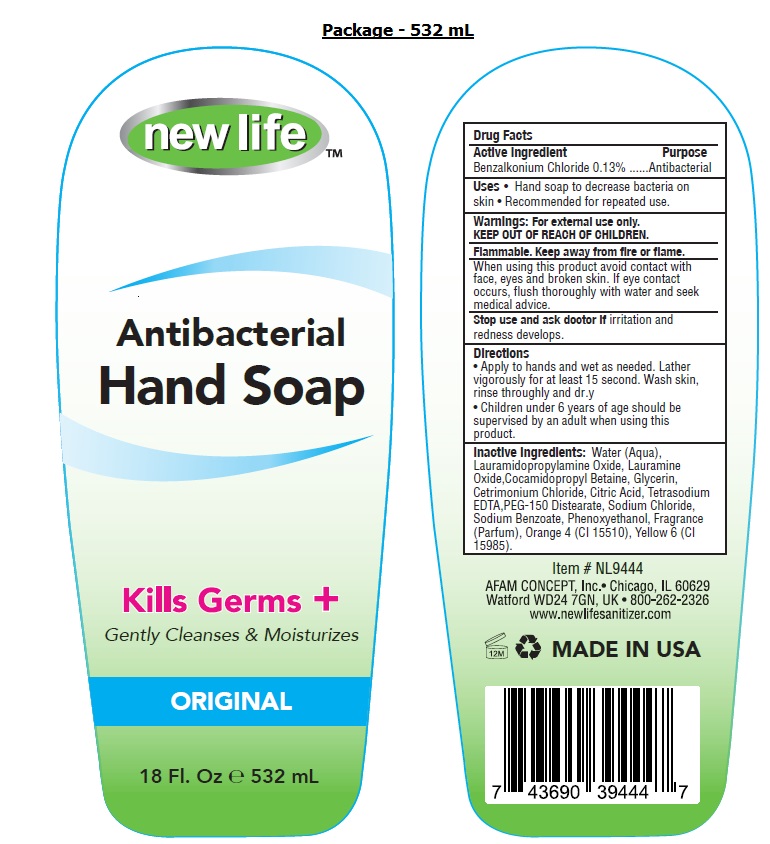 DRUG LABEL: New Life Antibacterial HandSoap
NDC: 49681-015 | Form: LIQUID
Manufacturer: New Life Products, Inc.
Category: otc | Type: HUMAN OTC DRUG LABEL
Date: 20230202

ACTIVE INGREDIENTS: BENZALKONIUM CHLORIDE 0.13 g/100 mL
INACTIVE INGREDIENTS: WATER; LAURAMIDOPROPYLAMINE OXIDE; LAURAMINE OXIDE; COCAMIDOPROPYL BETAINE; GLYCERIN; CETRIMONIUM CHLORIDE; CITRIC ACID MONOHYDRATE; EDETATE SODIUM; PEG-150 DISTEARATE; SODIUM CHLORIDE; SODIUM BENZOATE; PHENOXYETHANOL; D&C ORANGE NO. 4; FD&C YELLOW NO. 6

new lifeTM Antibacterial Hand Soap

Active Ingredient

Benzalkonium Chloride 0.13%

Purpose

Antibacterial

Uses

• Hand soap to decrease bacteria on skin. • Recommended for repeated use.

Warnings:

For external use only.

Flammable. Keep away from fire or flame.

When using this product avoid contact with face, eyes, and broken skin. If eye contact occurs, flush thoroughly with water and seek medical advice.

Stop use and ask doctor if irritation and redness develops.

KEEP OUT OF REACH OF CHILDREN.

Directions

• Apply to hands and wet as needed. Lather vigorously for at least 15 second. Wash skin, rinse thoroughly and dry

• Children under 6 years of age should be supervised by an adult when using this product.

Inactive Ingredients:

Water (Aqua), Lauramidopropylamine Oxide, Lauramine Oxide, Cocamidopropyl Betaine, Glycerin, Cetrimonium Chloride, Citric Acid, Tetrasodium EDTA, PEG-150 Distearate, Sodium Chloride, Sodium Benzoate, Phenoxyethanol, Fragrance (Parfum), Orange 4 (CI 15510), Yellow 6 (CI 15985).

Kills Germs +

Gently Cleanses & Moisturizes

ORIGINAL

AFAM CONCEPT, Inc. • Chicago, IL 60629

Watford WD24 7GN, UK • 800-262-2326

www.newlifesanitizer.com

cruelty free

MADE IN USA